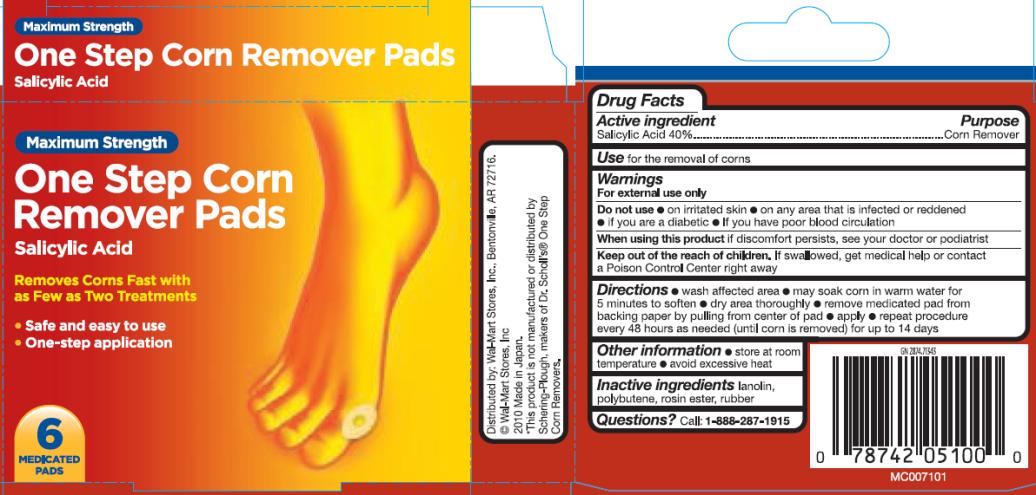 DRUG LABEL: Equate One Step Corn Remover Pad
NDC: 49035-152 | Form: LIQUID
Manufacturer: Wal-Mart Stores Inc.
Category: otc | Type: HUMAN OTC DRUG LABEL
Date: 20101007

ACTIVE INGREDIENTS: SALICYLIC ACID 40 mg/1 1
INACTIVE INGREDIENTS: LANOLIN; ROSIN

One Step Corn Remover Pad

Drug Facts

Active ingredient

Salicylic Acid 40%

Purpose

Corn Remover

Use

For the removal of corns

Warnings

For external use only

Do not use

- on irritated skin
- on any area that is infected or reddened
- if you are a diabetic
- if you have poor blood circulation

When using this product

if discomfort persists, see your doctor or podiatrist

Keep out of reach of children.

If swallowed, get medical help or contact a Poison Control Center right away.

Directions

- wash affected area
- may soak corn in warm water for 5 minutes to soften
- dry area thoroughly
- remove medicated pad from backing paper by pulling from center of pad
- apply
- repeat procedure every 48 hours as needed (until corn is removed) for up to 14 days

Other information

- store at room temperature
- avoid excessive heat

Inactive ingredients

lanolin, polybutene, rosin ester, rubber

Questions?

Call: 1-888-287-1915

PRINCIPAL DISPLAY PANEL

Maximum Strength
One Step Corn Remover Pads
Salicylic Acid
6 Medicated Pads